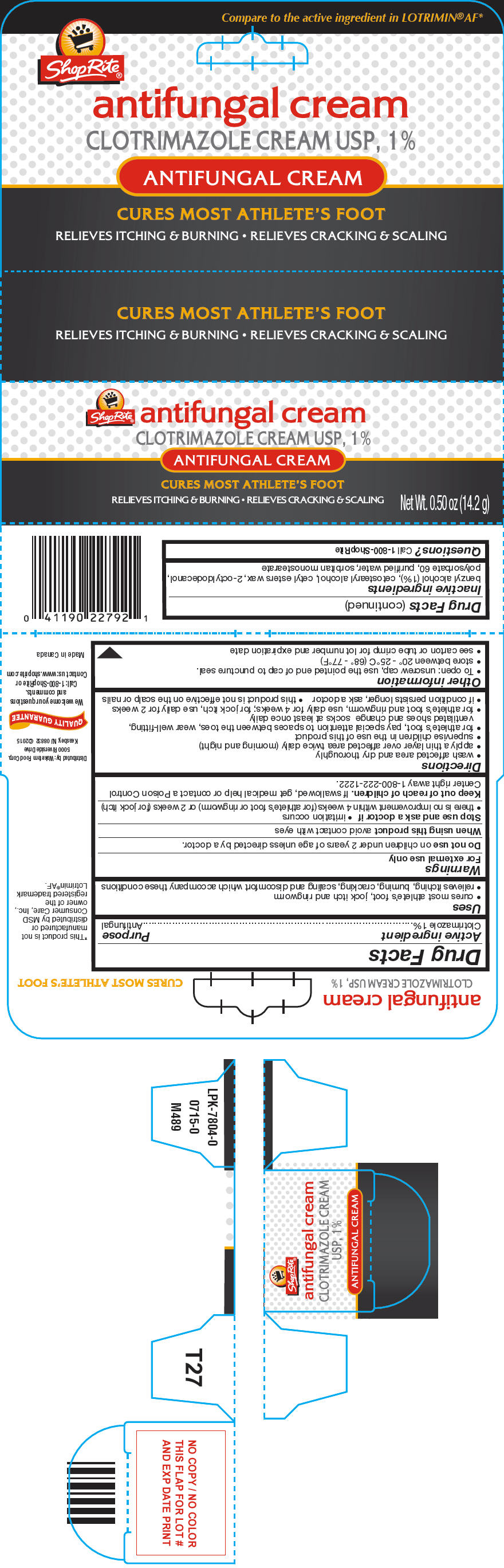 DRUG LABEL: ShopRite antifungal
NDC: 41190-002 | Form: CREAM
Manufacturer: WAKEFERN FOOD CORPORATION
Category: otc | Type: HUMAN OTC DRUG LABEL
Date: 20150807

ACTIVE INGREDIENTS: Clotrimazole 10 mg/1 g
INACTIVE INGREDIENTS: benzyl alcohol; cetostearyl alcohol; cetyl esters wax; octyldodecanol; polysorbate 60; water; sorbitan monostearate

ShopRite® antifungal cream

Drug Facts

Active ingredient

Clotrimazole 1%

Purpose

Antifungal

Uses

- cures most athlete's foot, jock itch and ringworm
- relieves itching, burning, cracking, scaling and discomfort which accompany these conditions

Warnings

For external use only

Do not use on children under 2 years of age unless directed by a doctor.

When using this product avoid contact with eyes

Stop use and ask a doctor if

- irritation occurs
- there is no improvement within 4 weeks (for athlete's foot or ringworm) or 2 weeks (for jock itch)

Keep out of reach of children. If swallowed, get medical help or contact a Poison Control Center right away 1-800-222-1222.

Directions

- wash affected area and dry thoroughly
- apply a thin layer over affected area twice daily (morning and night)
- supervise children in the use of this product
- for athlete's foot, pay special attention to spaces between the toes, wear well-fitting, ventilated shoes and change socks at least once daily
- for athlete's foot and ringworm, use daily for 4 weeks; for jock itch, use daily for 2 weeks
- if condition persists longer, ask a doctor
- this product is not effective on the scalp or nails

Other information

- To open: unscrew cap, use the pointed end of cap to puncture seal.
- store between 20° - 25°C (68° - 77°F)
- see carton or tube crimp for lot number and expiration date

Inactive ingredients

benzyl alcohol (1%), cetostearyl alcohol, cetyl esters wax, 2-octyldodecanol, polysorbate 60, purified water, sorbitan monostearate

Questions?

Call 1-800-ShopRite

Distributed by: Wakefern Food Corp.
5000 Riverside Drive
Keasbey, NJ 08832

PRINCIPAL DISPLAY PANEL - 14.2 g Tube Carton

ShopRite® antifungal cream
CLOTRIMAZOLE CREAM USP, 1%

ANTIFUNGAL CREAM

CURES MOST ATHLETE'S FOOT

RELIEVES ITCHING & BURNING • RELIEVES CRACKING & SCALING

Net Wt. 0.50 oz (14.2 g)